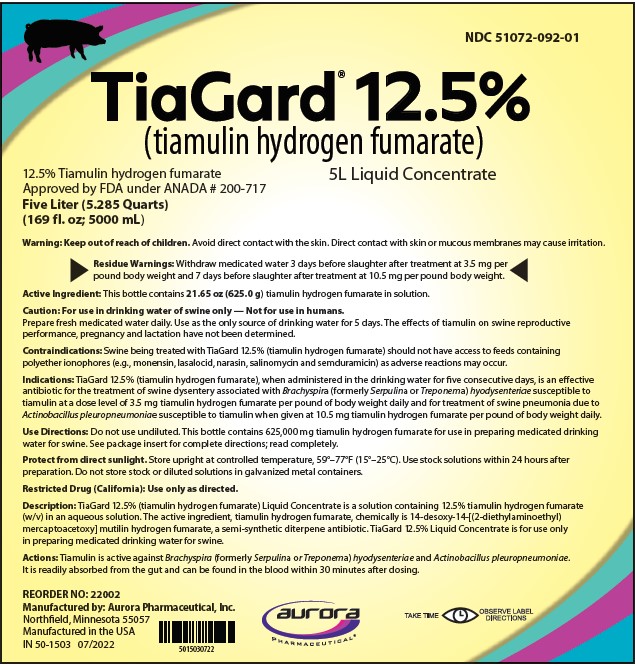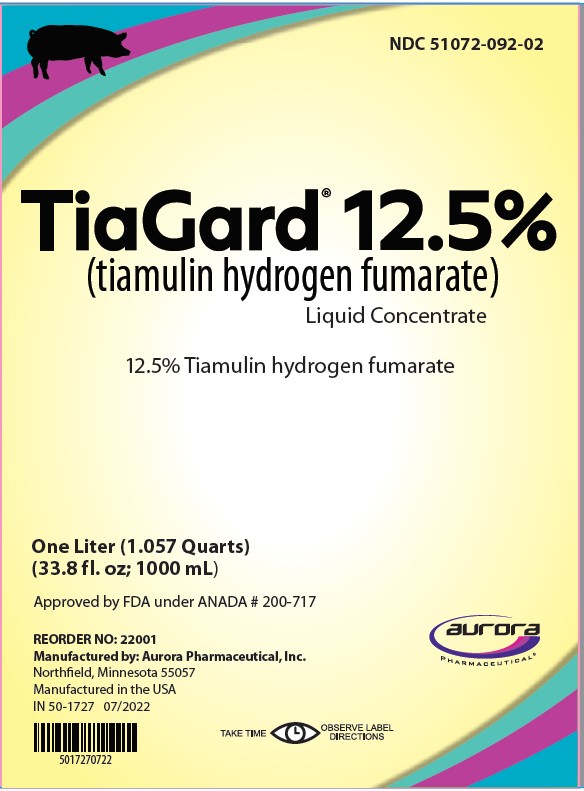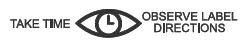 DRUG LABEL: TiaGard 12.5%
NDC: 51072-092 | Form: CONCENTRATE
Manufacturer: Aurora Pharmaceutical, Inc.
Category: animal | Type: OTC ANIMAL DRUG LABEL
Date: 20240619

ACTIVE INGREDIENTS: tiamulin fumarate 0.125 g/1 mL

TiaGard® 12.5%
(tiamulin hydrogen fumarate)

Liquid Concentrate

12.5% Tiamulin hydrogen fumarate

Approved by FDA under ANADA # 200-717

Description:

TiaGard 12.5% (tiamulin hydrogen fumarate) Liquid Concentrate is a solution containing 12.5% tiamulin hydrogen fumarate (w/v) in an aqueous solution. The active ingredient, tiamulin hydrogen fumarate, chemically is 14-desoxy-14-[(2-diethylaminoethyl) mercaptoacetoxy] mutilin hydrogen fumarate, a semi-synthetic diterpene antibiotic. TiaGard 12.5% Liquid Concentrate is for use only in preparing medicated drinking water for swine.

Actions:

Tiamulin is active against Brachyspira (formerly Serpulina or Treponema) hyodysenteriae and Actinobacillus pleuropneumoniae. It is readily absorbed from the gut and can be found in the blood within 30 minutes after dosing.

Indications:

TiaGard 12.5% (tiamulin hydrogen fumarate), when administered in the drinking water for five consecutive days, is an effective antibiotic for the treatment of swine dysentery associated with Brachyspira (formerly Serpulina or Treponema) hyodysenteriae susceptible to tiamulin at a dose level of 3.5 mg tiamulin hydrogen fumarate per pound of body weight daily and for treatment of swine pneumonia due to Actinobacillus pleuropneumoniae susceptible to tiamulin when given at 10.5 mg tiamulin hydrogen fumarate per pound of body weight daily.

Contraindications:

Swine being treated with TiaGard 12.5% (tiamulin hydrgen fumarate) should not have access to feeds containing polyether ionophores (e.g., monensin, lasalocid, narasin, salinomycin and semduramicin) as adverse reactions may occur.

Warning:

Keep out of reach of children. Avoid contact with skin. Direct contact with skin or mucous membranes may cause irritation.

Residue Warnings:

Withdraw medicated water 3 days before slaughter after treatment at 3.5 mg per pound and 7 days before slaughter following treatment at 10.5 mg per pound body weight.

Caution: For use in drinking water of swine only - Not for use in humans

Prepare fresh medicated water daily. Use as the only source of drinking water for 5 days. The effects of tiamulin on swine reproductive performance, pregnancy and lactation have not been determined.

Adverse Reactions:

Overdoses of tiamulin hydrogen fumarate have sometimes produced transitory salivation, vomiting and an apparent calming effect on the pig. If signs of toxicity occur, discontinue use of medicated water and replace with clean, fresh water. In rare cases, redness of the skin primarily over the ham and underline has been observed during medication. If these signs appear, discontinue use of this drug. Provide ample clean drinking water. Thoroughly rinse (hose down) the housing to remove urine and feces from animal contact surfaces or move the animals to clean pens. If the condition persists, consult your veterinarian. Studies to evaluate the safety of the water soluble form of tiamulin in breeding swine have not been done.

Use Directions:

The concentration of tiamulin hydrogen fumarate in the drinking water must be adjusted to compensate for variation in water consumption due to weight or size of the pig, environmental temperature and other factors. It is important that pigs receive the proper drug dose, 3.5 mg tiamulin hydrogen fumarate per pound for swine dysentery or 10.5 mg tiamulin hydrogen fumarate per pound for swine pneumonia, each day for 5 consecutive days.

Directions for preparing TiaGard 12.5% medicated solutions

Determine the amount of TiaGard 12.5% Liquid Concentrate needed to medicate the desired volume of drinking water at the proper concentration. Carefully measure out this amount, add it to the water and stir to thoroughly mix.

Number of pigs this bottle will treat for ONE day based on water consumption per pig |  | One Liter
Net tiamulin hydrogen fumarate content: |  | 125,000 mg
Diseases to be treated: |  | Swine Dysentery | Swine Pneumonia
Daily tiamulin hydrogen fumarate required per pound body weight: |  | 3.5 mg | 10.5 mg
Required treatment duration: |  | 5 days | 5 days
Pig Wt, lb | Water Intake, gal | # of pigs | # of pigs
20 | 0.3 - 0.5 | 1,786 | 595
45 | 0.4 - 1.1 | 794 | 265
75 | 0.7 - 1.5 | 476 | 159
125 | 1.0 - 2.0 | 286 | 95
180 | 1.2 - 3.0 | 198 | 66
Suggested final dilution of: | 1 bottle (1 Liter) | 550 gal | 183 gal
Suggested final dilution of: | 3 bottles (3 Liters) | 1650 gal | 550 gal
Suggested final dilution of: | 1/2 bottle (0.5 Liters) | 275 gal | 92 gal
Tiamulin hydrogen fumarate concentration per gallon at suggested final dilution* |  | 227 mg | 681 mg
Tiamulin hydrogen fumarate concentration per gallon at suggested final dilution* |  | (60 ppm) | (180 ppm)
1. Prepare fresh medicated drinking water every day for the 5 day treatment period.
2. Water medicated with TiaGard 12.5% should be the only source of drinking water during the treatment period.
*3. Increase or decrease dilution rate as required to obtain proper daily drug dose.

Directions for using TiaGard 12.5%

In medicated proportioners: One liter of TiaGard 12.5% Liquid Concentrate mixed with water to make 4.3 gallons of stock solution and this stock solution metered at one fluid ounce per gallon will provide 227 mg of tiamulin hydrogen fumarate per gallon to 550 gallons of drinking water for treatment of swine dysentery. Five liters of TiaGard 12.5% Liquid Concentrate mixed with water to make 21.5 gallons of stock solution and this stock solution metered at one fluid ounce per gallon will provide 227 mg of tiamulin hydrogen fumarate per gallon to 2750 gallons of drinking water for treatment of swine dysentery Three liters of TiaGard 12.5% Liquid Concentrate mixed with water to make 4.3 gallons of stock solution and this stock solution metered at one fluid ounce per gallon will provide 681 mg tiamulin hydrogen fumarate per gallon to a total of 550 gallons of drinking water for treatment of swine pneumonia. Fifteen liters of TiaGard 12.5% Liquid Concentrate mixed with water to make 21.5 gallons of stock solution and this stock solution metered at one fluid ounce per gallon will provide 681 mg tiamulin hydrogen fumarate per gallon to a total of 2750 gallons of drinking water for treatment of swine pneumonia. In barrels or tanks: One liter (1000 mL) of TiaGard 12.5% Liquid Concentrate will medicate 550 gallons of drinking water at 227 mg per gallon for treatment of swine dysentery or 183 gallons at 681 mg per gallon for treatment of swine pneumonia at 381 mg per gallon for treatment of swine pneumonia. Measure TiaGard 12.5% Liquid Concentrate carefully, pour into the proper amount of water and thoroughly mix. The concentration of tiamulin hydrogen fumarate in the stock solution and in the drinking water delivered must be adjusted to compensate for variation in water consumption by pigs due to body weight, environmental and other factors. It is important that the pigs receive the proper drug dose of 3.5 mg of tiamulin hydrogen fumarate per pound of body weight daily for 5 consecutive days for treatment of swine dysentery or a dose of 10.5 mg per pound body weight daily for 5 consecutive days for treatment of swine pneumonia. Attention: If no response to treatment is obtained within 5 days re-establish the diagnosis. Failure of response may be related to the presence of non-susceptible organisms of other complicating disease conditions. Because of the tendency for the disease to recur on premises with a history of swine dysentery or with swine pneumonia, a control program should be implemented after treatment. Drugs are not substitutes for proper sanitary measures or good management, but should be used in conjunction with such practices.

How supplied:

Container Size | Active Ingredients
1 Liter bottles | 12.5% (125.0 g)
(33.8 fl oz; 1000 mL) | Tiamulin hydrogen fumarate
5 Liter bottles (169 fl oz; 5000 mL) | 12.5% (125.0 g)Tiamulin hydrogen fumarate

STORAGE AND HANDLING

Protect from direct sunlight. Store at controlled room temperature, 59 °–77 °F (15 °–25 °C). Use stock solutions within 24 hours after preparation. Do not store stock or diluted solutions in galvanized metal containers.

Observe expiration date.

To report suspected adverse drug events, for technical assistance or to obtain a copy of the Safety Data Sheet, contact Aurora Pharmaceutical at 1-888-215-1256 or http://www.aurorapharmaceutical.com. For additional information about adverse drug experience reporting for animal drugs, contact FDA at 1-888-FDA-VETS or http://www.fda.gov/reportanimalae.

Restricted Drug (California): Use only as directed.

Principal Display Panel - TiaGard 12.5% 1000 mL Bottle Label

NDC 51072-092-02

TiaGard® 12.5%

(tiamulin hydrogen fumarate)

Liquid Concentrate

12.5% Tiamulin hydrogen fumarate

Approved by FDA under ANADA # 200-717

One Liter (1.057 Quarts)

(33.8 fl oz; 1000 mL)

REORDER NO: 22001

MANUFACTURED BY:
Aurora Pharmaceutical, Inc.NORTHFIELD, MINNESOTA 55057
1-888-215-1256
www.aurorapharmaceutical.com

IN 50-1727 07/2022

Principal Display Panel - TiaGard 12.5% 5000 mL Bottle Label

NDC 51072-092-01

TiaGard® 12.5%

(tiamulin hydrogen fumarate)

Liquid Concentrate

12.5% Tiamulin hydrogen fumarate

Approved by FDA under ANADA # 200-717

One Liter (5.285 Quarts)

(169 fl oz; 5000 mL)

REORDER NO: 22002

MANUFACTURED BY:
Aurora Pharmaceutical, Inc.NORTHFIELD, MINNESOTA 55057
1-888-215-1256
www.aurorapharmaceutical.com

IN 50-1503 07/2022